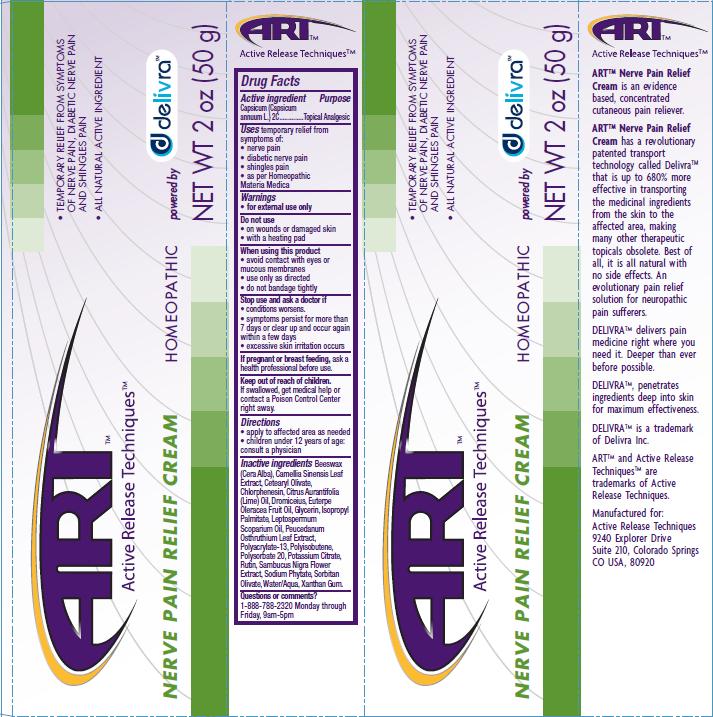 DRUG LABEL: Nerve Pain Relief
NDC: 76029-002 | Form: CREAM
Manufacturer: Active Release Techniques
Category: homeopathic | Type: HUMAN OTC DRUG LABEL
Date: 20110330

ACTIVE INGREDIENTS: CAPSICUM 2 [hp_C]/50 g
INACTIVE INGREDIENTS: WHITE WAX; BANCHA TEA LEAF/TWIG; CETEARYL OLIVATE; CHLORPHENESIN; CITRUS AURANTIIFOLIA LEAF OIL; ACAI OIL; ISOPROPYL PALMITATE; MANUKA OIL; PEUCEDANUM OSTRUTHIUM LEAF; POLYSORBATE 20; POTASSIUM CITRATE; RUTIN; SAMBUCUS NIGRA FLOWER; SORBITAN OLIVATE; WATER; XANTHAN GUM

ACTIVE INGREDIENT

Capsicum (Capsicum annuum L) 2C

PURPOSE

Topical Analgesic

INDICATIONS AND USAGE

temporary relief from symptoms of:

- nerve pain
- diabetic nerve pain
- shingles pain

as per Homeopathic Materia Medica

WARNINGS

- for external use only

DO NOT USE

- on wounds or damaged skin
- with a heating pad

WHEN USING

- avoid contact with eyes or mucous membranes
- use only as directed
- do not bandage tightly

STOP USE

- condition worsens
- symptoms persist for more than 7 days or clear up and occur again within a few days
- excessive skin irritation occurs

PREGNANCY OR BREAST FEEDING

If pregnant or breast feeding, ask a health professional before use.

Keep out of reach of children.
If swallowed, get medical help or contact a Poison Control Center right away.

DOSAGE AND ADMINISTRATION

- apply to affected area as needed
- children under 12 years of age: consult a physician

INACTIVE INGREDIENT

Beeswax (Cera Alba), Camellia Sinensis Leaf Extract, Cetearyl Olivate, Chlrophenesin, Citrus Aurantifolia (Lime) Oil, Dromiceius, Euterpe Oleracea Fruit Oil, Glycerin, Isopropyl Palmitate, Leptospermum Scoparium Oil, Peucedanum Osthruthium Leaf Extract, Polyacrylate-13, Polyisobutene, Polysorbate 20, Potassium Citrate, Rutin, Sambucus Nigra Flower Extract, Sodium Phytate, Sorbitan Olivate, Water/Aqua, Xanthan Gum

QUESTIONS

1-888-788-2320 Monday through Friday, 9am-5pm

PACKAGE LABEL

- Temporary relief from symptoms of nerve pain, diabetic nerve pain and shingles pain
- All natural active ingredient